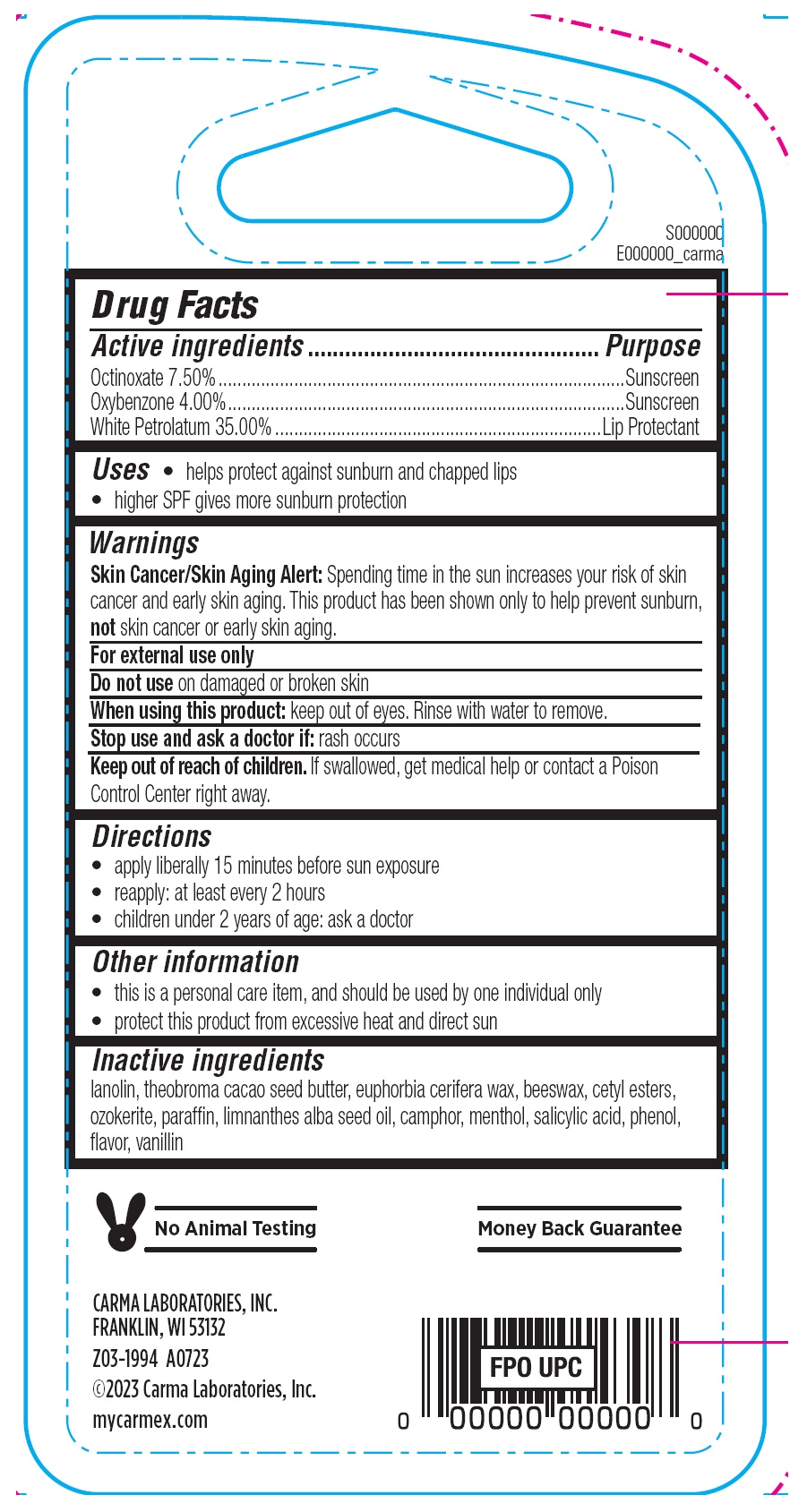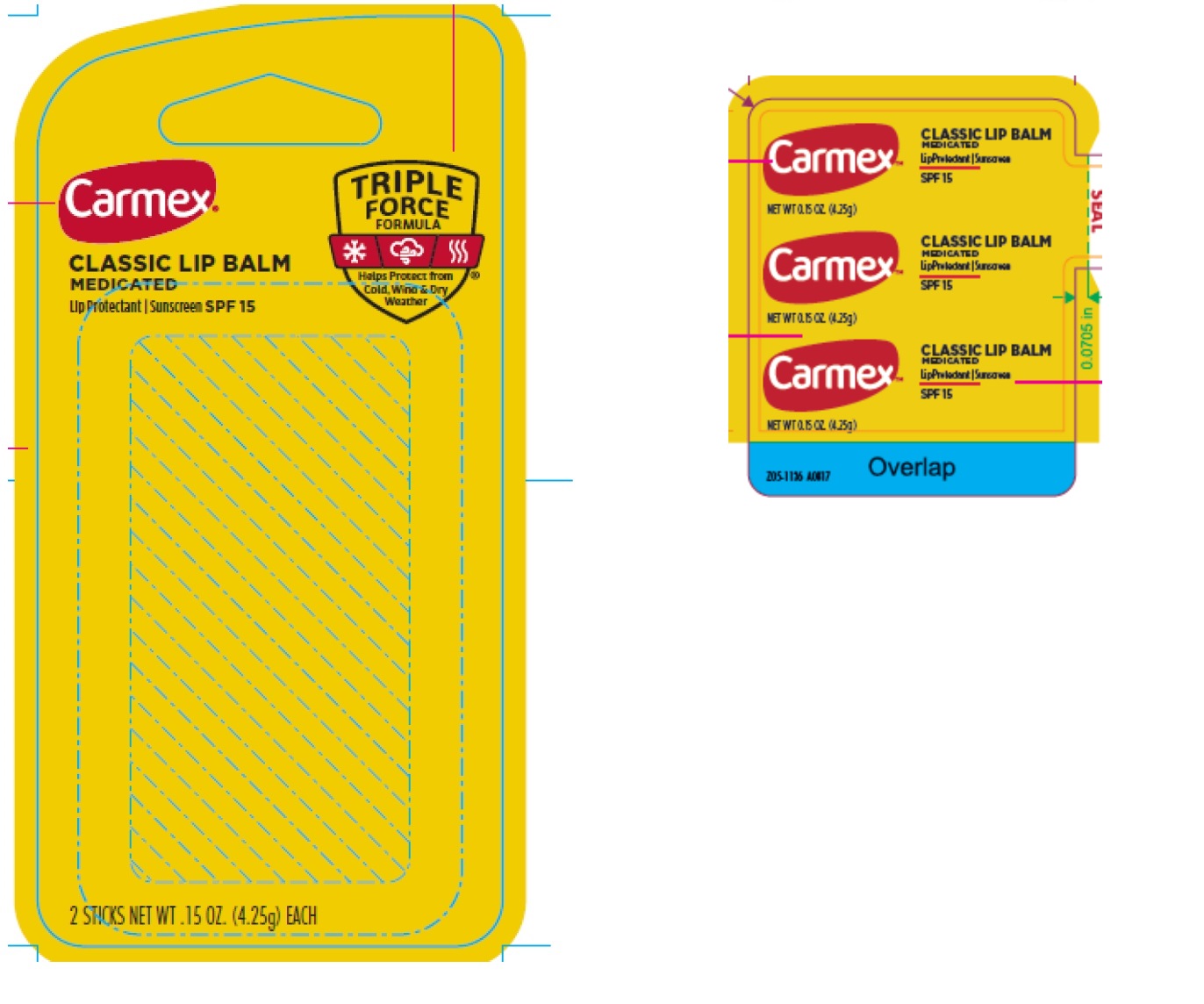 DRUG LABEL: Carmex Classic Lip Balm Medicated SPF15 Triple Force Formula
NDC: 10210-0066 | Form: SALVE
Manufacturer: Carma Laboratories, Inc.
Category: otc | Type: HUMAN OTC DRUG LABEL
Date: 20240402

ACTIVE INGREDIENTS: OCTINOXATE 75 mg/1 g; OXYBENZONE 40 mg/1 g; WHITE PETROLATUM 350 mg/1 g
INACTIVE INGREDIENTS: LANOLIN; YELLOW WAX; CETYL ESTERS WAX; PARAFFIN; MEADOWFOAM SEED OIL; CAMPHOR (SYNTHETIC); MENTHOL; SALICYLIC ACID; PHENOL; VANILLIN

Carmex Classic Lip Balm Medicated SPF15 Triple Force Formula

Active ingredients

Octinoxate 7.50%
Oxybenzone 4.00%
White Petrolatum 35.00%

Purpose

Sunscreen

Suncreen

Lip Protectant

Uses

- helps protect against sunburn and chapped lips
- higher SPF gives more sunburn protection

Warnings

Skin Cancer/Skin Aging Alert:Spending time in the sun increases your risk of skin cancer and early skin aging. This product has been shown only to help prevent sunburn, not skin cancer or early skin aging.

For external use only

Do not use

on damaged or broken skin

When using this product:

keep out of eyes. Rinse with water to remove.

Stop use and ask a doctor if:

rash occurs

Keep out of reach of children.

If swallowed, get medical help or contact a Poison Control Center right away.

Directions

- apply liberally 15 minutes before sun exposure
- reapply: at least every 2 hours
- children under 2 years of age: ask a doctor

Other information

- this is a personal care item, and should be used by one individual only
- protect this product from excessive heat and direct sun

Inactive ingredients

lanolin, theobroma cacao seed butter, euphorbia cerifera wax, beeswax, cetyl esters, ozokerite, paraffin, limnanthes alba seed oil, camphor, menthol, salicylic acid, phenol, flavor, vanillin